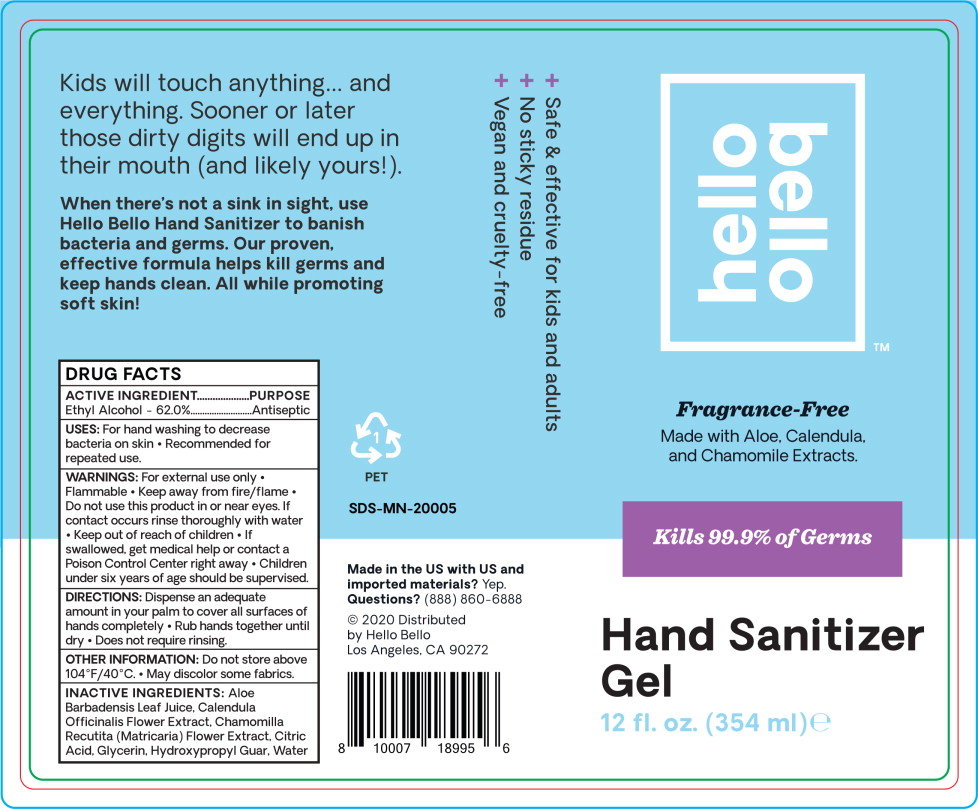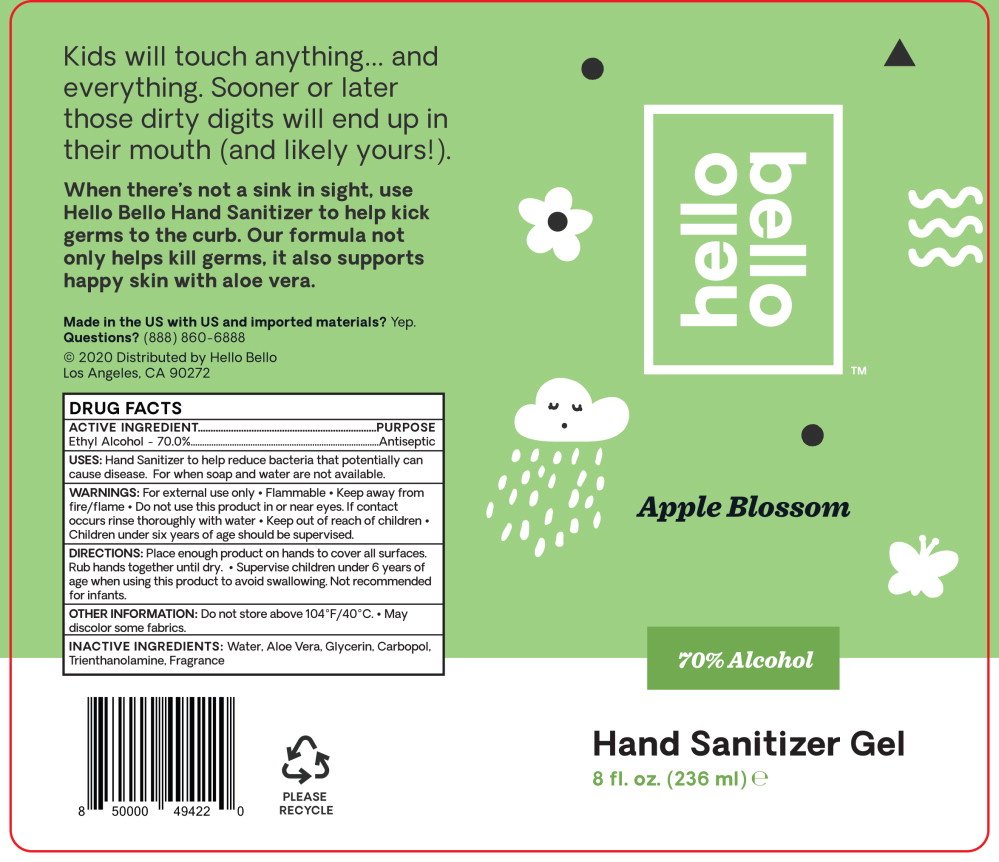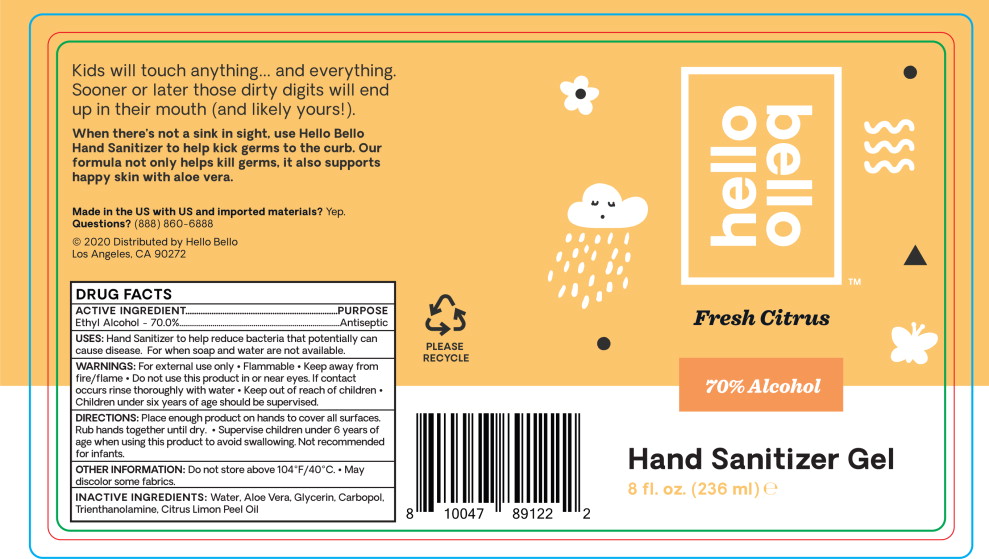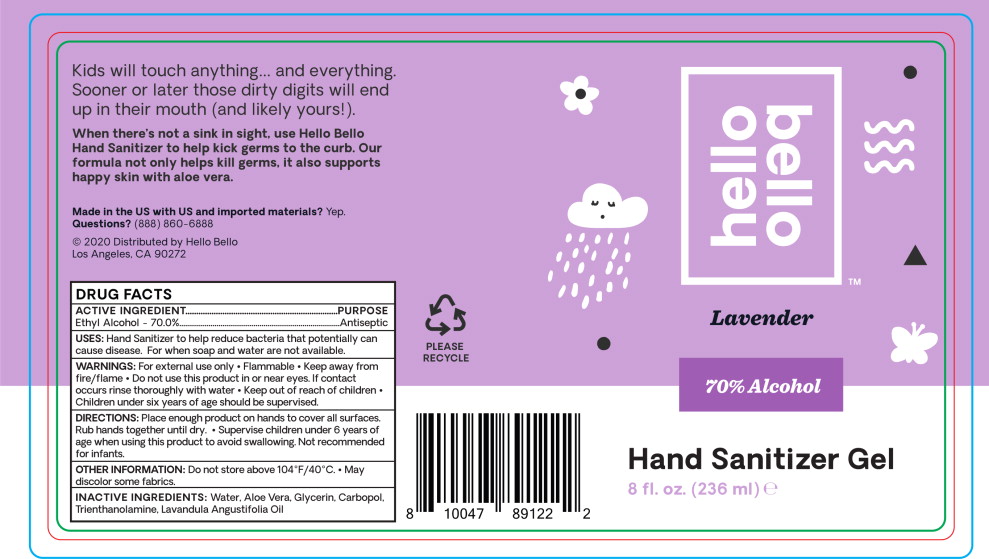 DRUG LABEL: Alcohol
NDC: 73418-035 | Form: GEL
Manufacturer: Hello Bello
Category: otc | Type: HUMAN OTC DRUG LABEL
Date: 20210209

ACTIVE INGREDIENTS: Alcohol 62 mL/100 mL
INACTIVE INGREDIENTS: Aloe Vera Leaf; Calendula Officinalis Flower; Chamomile; Citric Acid Monohydrate; Glycerin; Guaraprolose (1300 MPA.S AT 1%); Water

DRUG FACTS

ACTIVE INGREDIENT.

Ethyl Alcohol - 70.0%

PURPOSE

Antiseptic

USES:

Hand Sanitizer to help reduce bacteria that potentially can cause disease. For when soap and water are not available.

WARNINGS:

For external use only

- Flammable
- Keep away from fire/flame

- Do not use this product in or near eyes. If contact occurs rinse thoroughly with water

- Keep out of reach of children
- Children under six years of age should be supervised.

DIRECTIONS:

Place enough product on hands to cover all surfaces. Rub hands together until dry.

- Supervise children under 6 years of age when using this product to avoid swallowing. Not recommended for infants.

OTHER INFORMATION:

Do not store above 104°F/40°C. • May discolor some fabrics.

INACTIVE INGREDIENTS:

Water, Aloe Vera, Glycerin, Carbopol, Trienthanolamine, Fragrance

Principal Display Panel – 354 mL Bottle Label

hello
bello™

Fragrance-Free

Made with Aloe, Calendula,
and Chamomile Extracts.

Kills 99.9% of Germs

Hand Sanitizer
Gel

12 fl. oz. (354 ml) e

Principal Display Panel – 236 mL Bottle Label

hello
bello™

Apple Blossom

70% Alcohol

Hand Sanitizer Gel

8 fl. oz. (236 ml) e

Principal Display Panel – 236 mL Bottle Label

hello
bello™

Fresh Citrus

70% Alcohol

Hand Sanitizer Gel

8 fl. oz. (236 ml) e

Principal Display Panel – 236 mL Bottle Label

hello
bello™

Lavender

70% Alcohol

Hand Sanitizer Gel

8 fl. oz. (236 ml) e